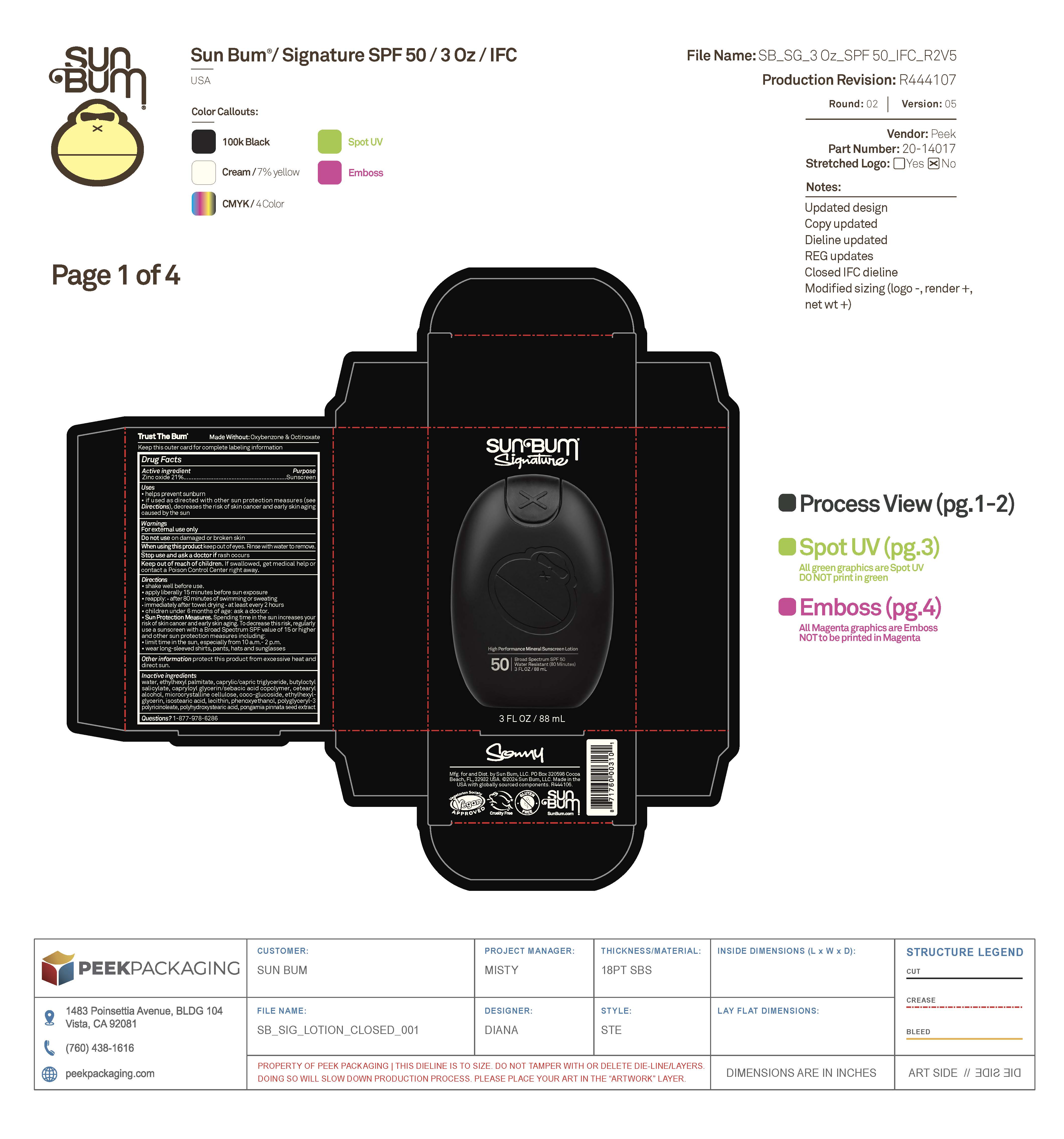 DRUG LABEL: Sun Bum Signature High Performance Mineral Sunscreen Broad Spectrum SPF 50 New
NDC: 69039-770 | Form: LOTION
Manufacturer: Sun Bum, LLC
Category: otc | Type: HUMAN OTC DRUG LABEL
Date: 20250819

ACTIVE INGREDIENTS: ZINC OXIDE 210 mg/1 mL
INACTIVE INGREDIENTS: WATER; MICROCRYSTALLINE CELLULOSE; POLYHYDROXYSTEARIC ACID (2300 MW); COCO-GLUCOSIDE; CETEARYL ALCOHOL; PHENOXYETHANOL; CAPRYLIC/CAPRIC TRIGLYCERIDE; BUTYLOCTYL SALICYLATE; CAPRYLOYL GLYCERIN/SEBACIC ACID COPOLYMER (2000 MPA.S); PONGAMIA PINNATA SEED; ISOSTEARIC ACID; LECITHIN, SUNFLOWER; POLYGLYCERYL-3 PENTARICINOLEATE; ETHYLHEXYLGLYCERIN; ETHYLHEXYL PALMITATE

Sun Bum Signature High Performance Mineral Sunscreen Broad Spectrum SPF 50 New

Active Ingredients

ZINC OXIDE 21%

Purpose

Sunscreen

Uses

• helps prevent sunburn • if used as directed with other sun protection measures, (see Directions) decreases the risk of skin cancer and early skin aging caused by the sun

Warnings

For external use only

Do not use on damaged or broken skin

When using this product keep out of eyes. Rinse with water to remove.

Stop use and ask a doctor if rash occurs

Keep out of reach of children. If swallowed, get medical help or contact a Poison Control Center right away.

Warnings

Keep Out Of Reach Of Children

Directions

• shake well before use

• apply liberally 15 minutes before sun exposure

• reapply: • after 80 minutes of swimming or sweating • immediately after towel drying • at least every 2 hours

• children under 6 months of age: ask a doctor

• Sun Protection Measures. Spending time in the sun increases your risk of skin cancer and early skin aging. To decrease this risk, regularly use a sunscreen with a Broad Spectrum SPF value of 15 or higher and other sun protection measures including:

• limit time in the sun, especially from 10 a.m.- 2 p.m.

• wear long-sleeved shirts, pants, hats and sunglasses

Directions

• shake well before use

• apply liberally 15 minutes before sun exposure

Other Information

protect this product from excessive heat and direct sun

Inactive Ingredients

WATER, ETHYLHEXYL PALMITATE, CAPRYLIC/CAPRIC TRIGLYCERIDE, BUTYLOCTYL SALICYLATE, CAPRYLOYL GLYCERIN/SEBACIC ACID COPOLYMER, CETEARYL ALCOHOL, MICROCRYSTALLINE CELLULOSE, COCO-GLUCOSIDE, ETHYLHEXYLGLYCERIN, ISOSTEARIC ACID, LECITHIN, PHENOXYETHANOL, POLYGLYCERYL-3 PENTARICINOLEATE, POLYHYDROXYSTEARIC ACID, PONGAMIA PINNATA SEED

Questions?

1-877-978-6286